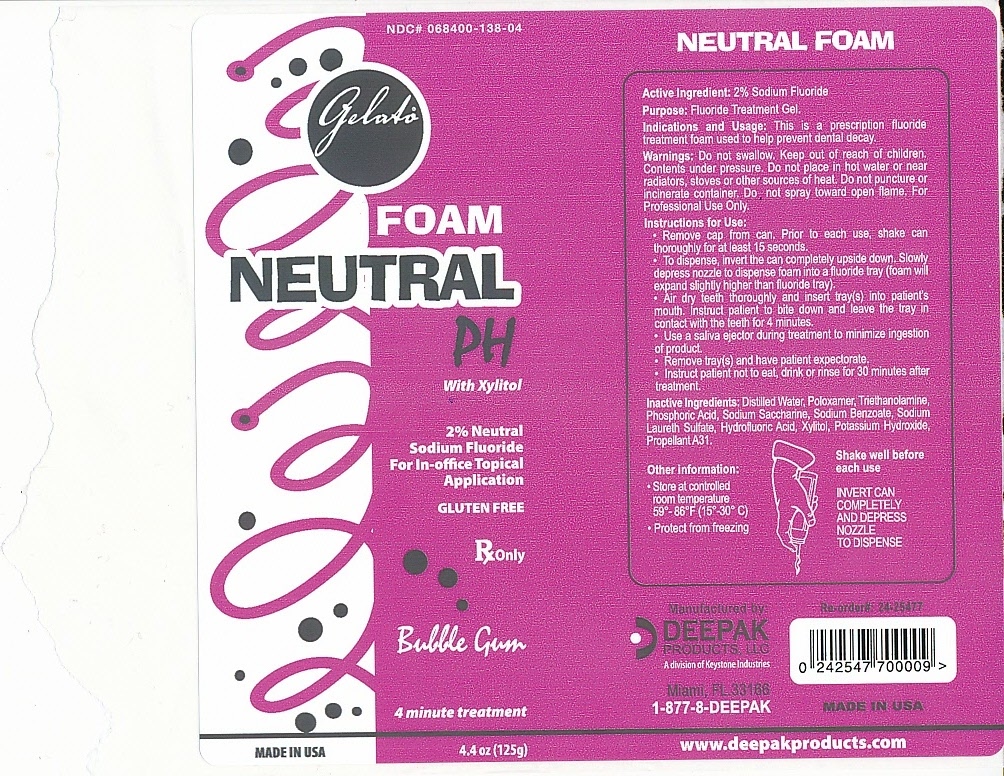 DRUG LABEL: Gelato Neutral PH
NDC: 68400-138 | Form: AEROSOL, FOAM
Manufacturer: Deepak Products, inc.
Category: prescription | Type: HUMAN PRESCRIPTION DRUG LABEL
Date: 20110811

ACTIVE INGREDIENTS: SODIUM FLUORIDE 2.5 g/125 g
INACTIVE INGREDIENTS: WATER; POLOXAMER 407; DECYL GLUCOSIDE; SODIUM LAURETH SULFATE; TROLAMINE; PHOSPHORIC ACID; SACCHARIN SODIUM; SODIUM BENZOATE; XYLITOL; HYDROFLUORIC ACID; POTASSIUM HYDROXIDE; DMDM HYDANTOIN

INDICATIONS AND USAGE

This is a prescription fluoride treatment foam used to help prevent dental decay.

WARNINGS

Do not swallow. Keep out of reach of children. Contents under pressure. Do not place in hot water or near radiators, stoves or other sources of heat. Do not puncture on incinerate container. Do not spray toward open flame. For professional use only.

INACTIVE INGREDIENT

Distilled water, Polaxamer, Triethanolamine, Phosphoric Acid, Sodium Saccharine, Sodium Laureth Sulfate, Hydrofluoric Acid, Xylitol, Potassium Hydroxide, Propellant A31.

STORAGE AND HANDLING

- Store at controlled room temperature 59-86 F (15-30 C)
- Protect from freezing